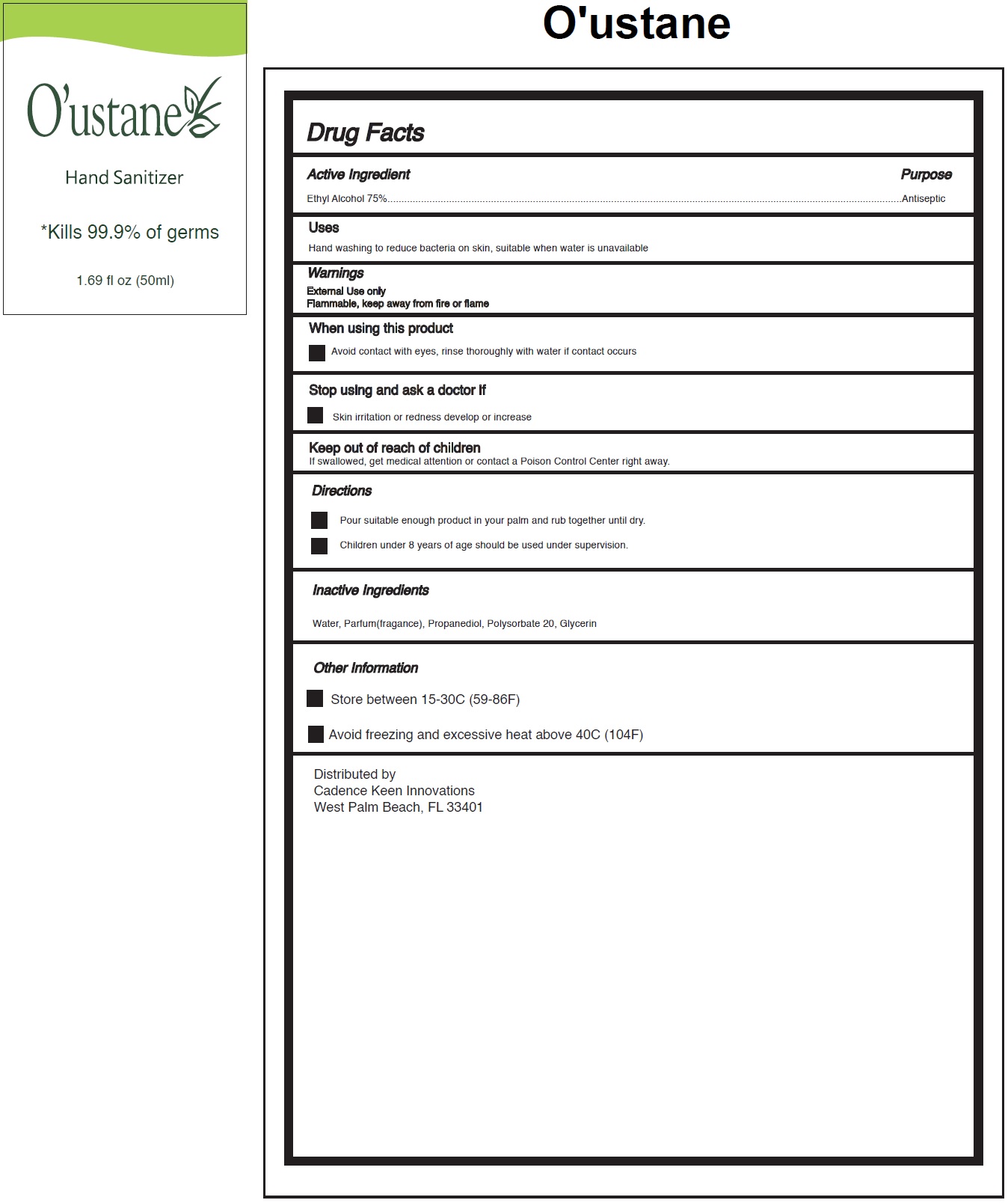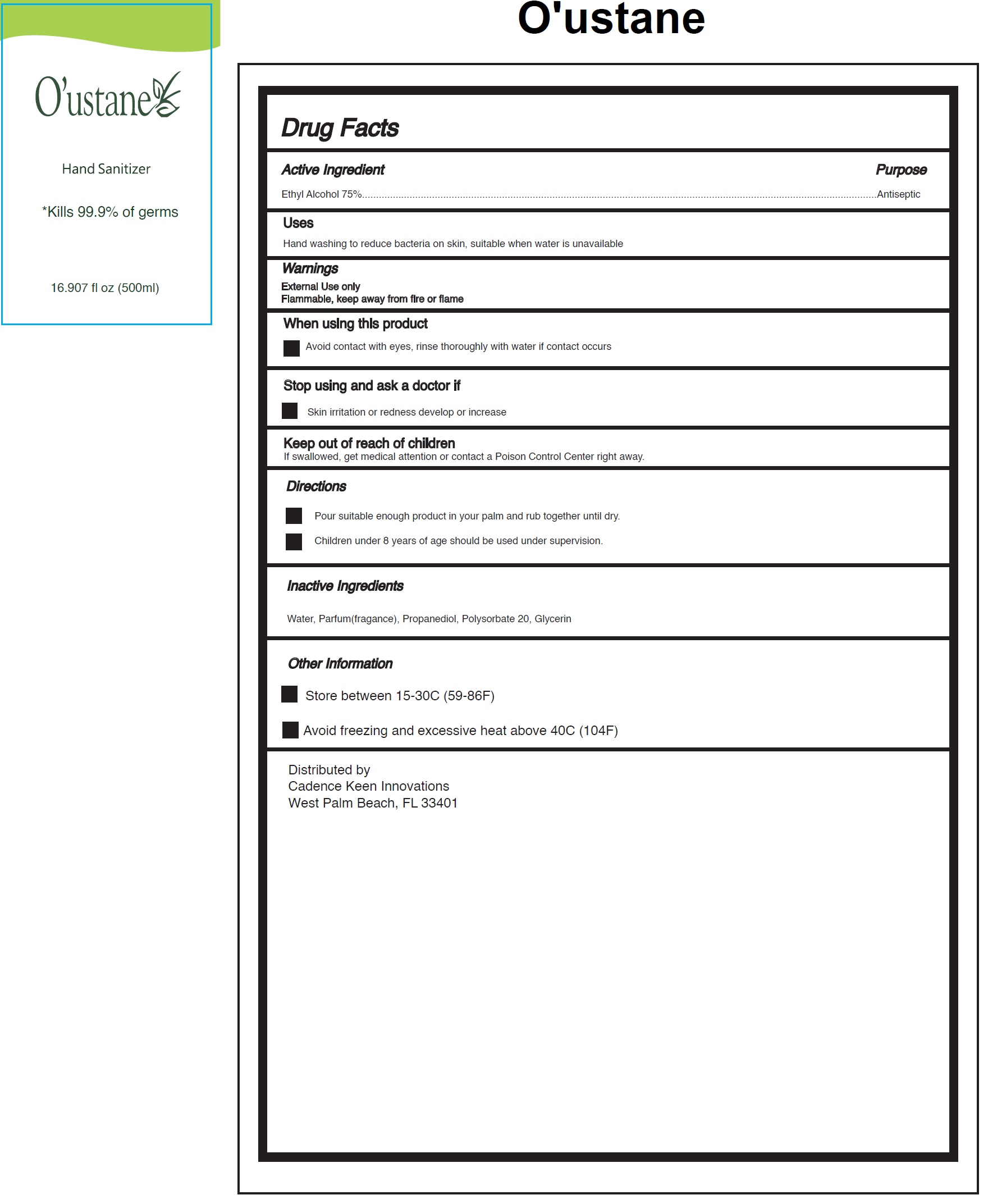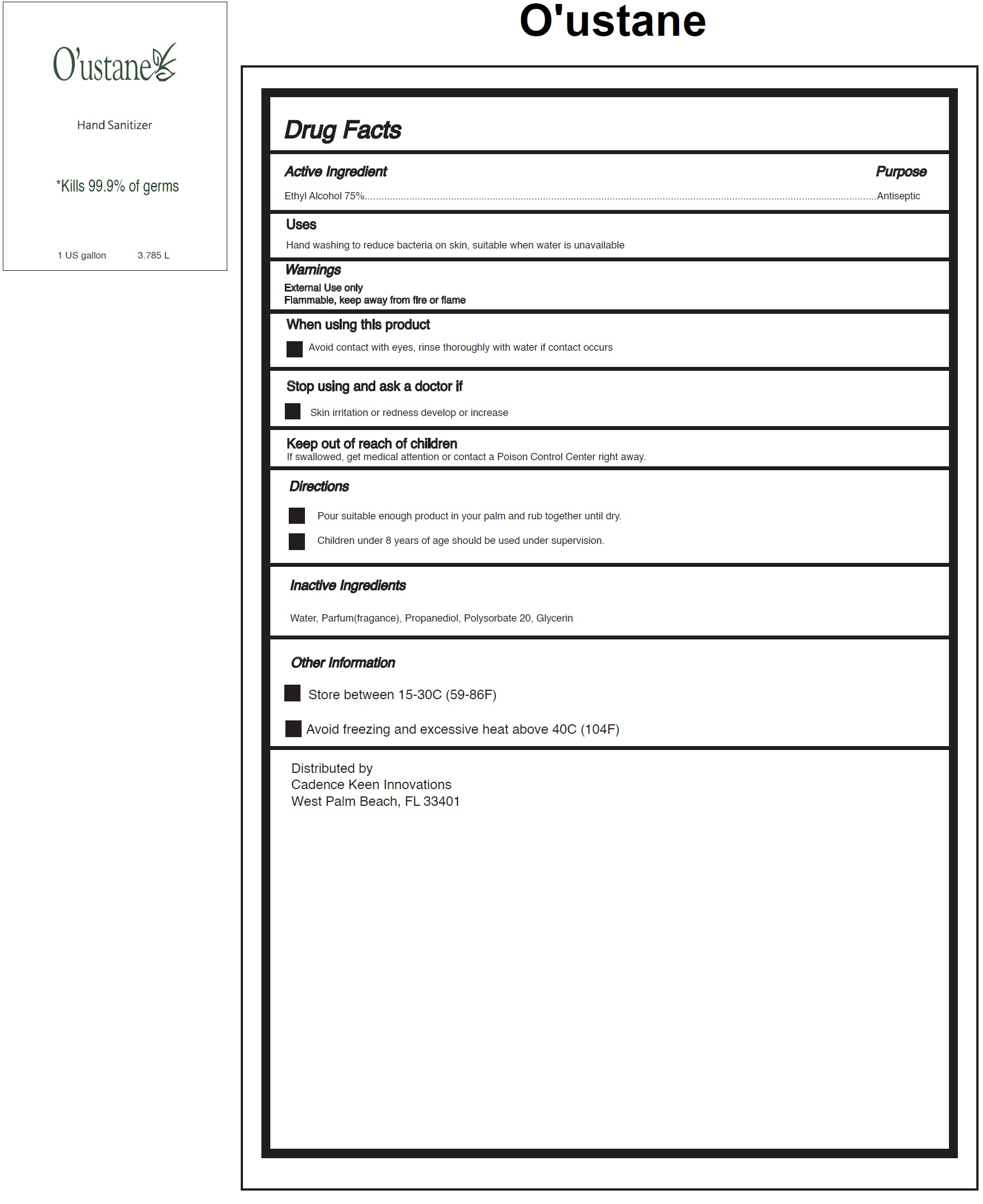 DRUG LABEL: Oustane Hand Sanitizer
NDC: 79128-000 | Form: GEL
Manufacturer: Cadence Keen Innovations, Inc.
Category: otc | Type: HUMAN OTC DRUG LABEL
Date: 20200629

ACTIVE INGREDIENTS: ALCOHOL 0.75 mL/1 mL
INACTIVE INGREDIENTS: WATER; PROPANEDIOL; POLYSORBATE 20; GLYCERIN

O'ustane Hand Sanitizer

Active Ingredient

Ethyl Alcohol 75%

Purpose

Antiseptic

Uses

Hand washing to reduce bacteria on skin, suitable when water is unavailable

Warnings

External Use only
Flammable, keep away from fire or flame

When using this product

Avoid contact with eyes, rinse thoroughly with water if contact occurs

Stop using and ask a doctor if

Skin irritation or redness develop or increase

Keep out of reach of children

If swallowed, get medical attention or contact a Poison Control Center right away.

Directions

- Pour suitable enough product in your palm and rub together until dry.
- Children under 8 years of age should be used under supervision.

Inactive Ingredients

Water, Parfum(fragance), Propanediol, Polysorbate 20, Glycerin

Other Information

- Store between 15-30C (59-86F)
- Avoid freezing and excessive heat above 40C (104F)